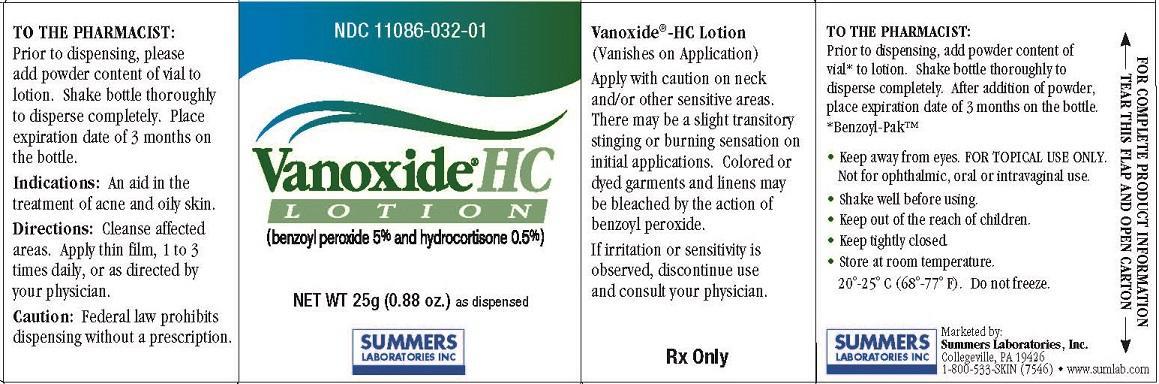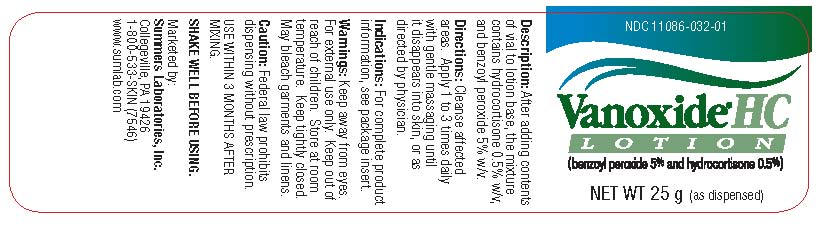 DRUG LABEL: VANOXIDE


NDC: 11086-032 | Form: LOTION
Manufacturer: Summers Laboratories Inc
Category: prescription | Type: HUMAN PRESCRIPTION DRUG LABEL
Date: 20231009

ACTIVE INGREDIENTS: BENZOYL PEROXIDE 5 g/100 g; HYDROCORTISONE 0.5 g/100 g

SUMMERS LABS (as PLD) - VANOXIDE (11086-032)

ACTIVE INGREDIENTS:

BENZOYL PEROXIDE 5%

HYDROCORTISONE 0.5%

WARNINGS

Apply with caution on neck and/or other sensitive areas. There may be a slight transitory stinging or burning sensation on initial applications. Colored or dyed garments and linens may be bleached by the action of benzoyl peroxide. If irritation or sensitivity is
observed, discontinue use and consult your physician.

KEEP OUT OF REACH OF CHILDREN.

DOSAGE AND ADMINISTRATION

TO THE PHARMACIST:
Prior to dispensing, add powder content of vial* to lotion. Shake bottle thoroughly to disperse completely. After addition of powder, place expiration date of 3 months on the bottle.
*Benzoyl-Pak™

INDICATIONS AND USAGE

- Keep away from eyes. FOR TOPICAL USE ONLY.Not for ophthalmic, oral or intravaginal use.
- Shake well before using.
- Keep tightly closed.
- Store at room temperature. 20°-25° C (68°-77° F). Do not freeze.